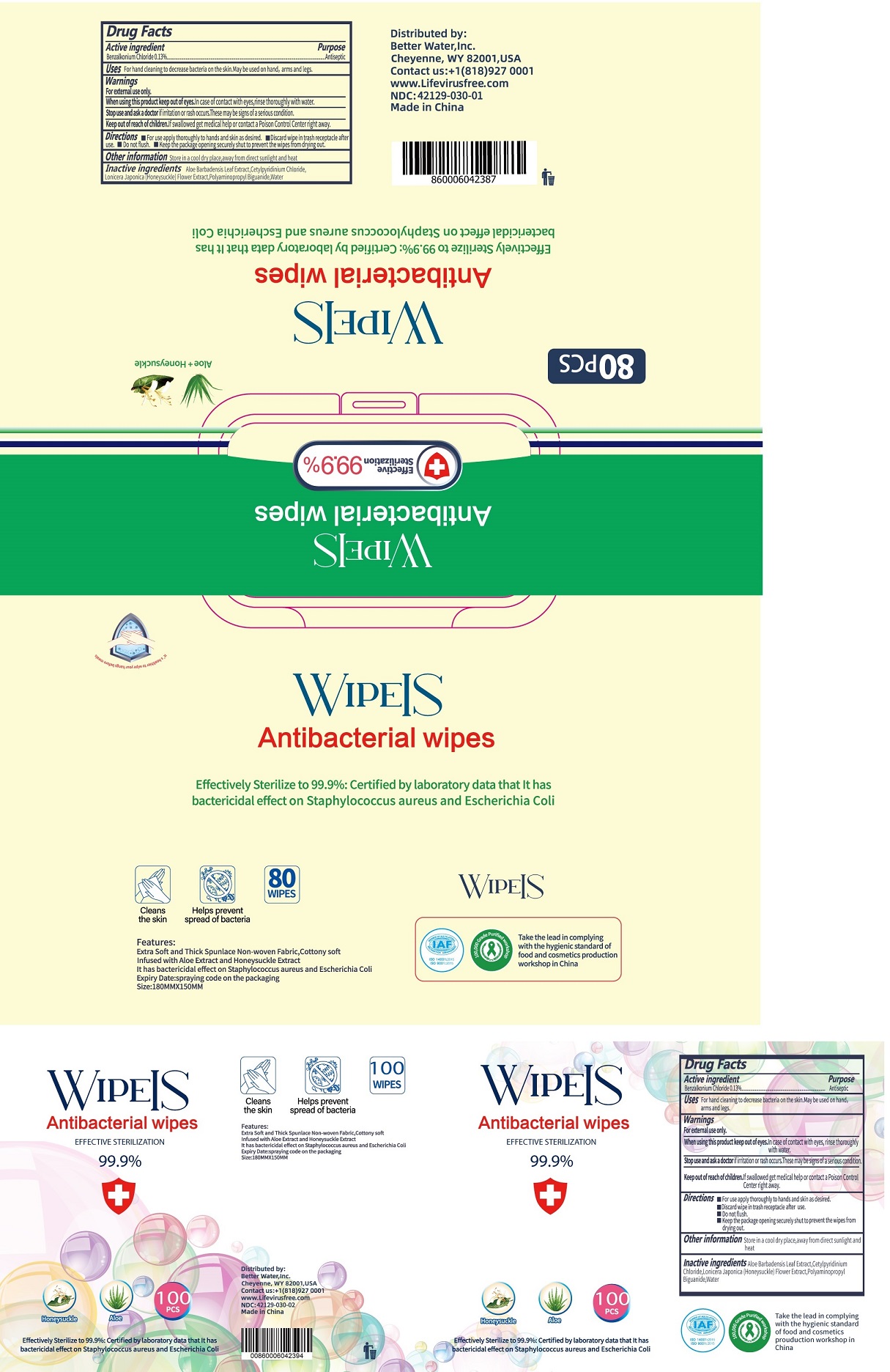 DRUG LABEL: Antibacterial Wipes
NDC: 42129-030 | Form: CLOTH
Manufacturer: Fustin(Xiamen) Commodity Co., ltd
Category: otc | Type: HUMAN OTC DRUG LABEL
Date: 20201228

ACTIVE INGREDIENTS: BENZALKONIUM CHLORIDE 0.13 1/100 1
INACTIVE INGREDIENTS: WATER; CETYLPYRIDINIUM CHLORIDE; LONICERA JAPONICA FLOWER; POLYAMINOPROPYL BIGUANIDE

wipes

Active Ingredient

BENZALKONIUM CHLORIDE .......... 0.13%

Purpose

Antiseptic

Warnings

For external use only.

When using this product. In case of contact with eyes, rinse thoroughly with water

Stop use and ask a doctor if irritation or rash occurs. These may be signs of a serious condition.

Other information

Store in a cool dry place, away from direct sunlight and heat.

INDICATIONS AND USAGE

For hand cleaning to decrease bacteria on the skin. May be used on hands, arms and legs.

Keep out of reach of children. If swallowed, get medical help or contact a Poison Control Center right away.

Directions

- For use apply thoroughly to hands and skin as desired.
- Discard wipe in trash receptacle after use.
- Do not flush.
- Keep the package opening securely shut to prevent the wipes from drying out.

Inactive ingredients

Aloe Barbadensis Leaf Extract, Cetylpyridinium Chloride, Lonicera Japonica (Honeysuckle) Flower Extract, Polyaminopropyl Biguanide, Water